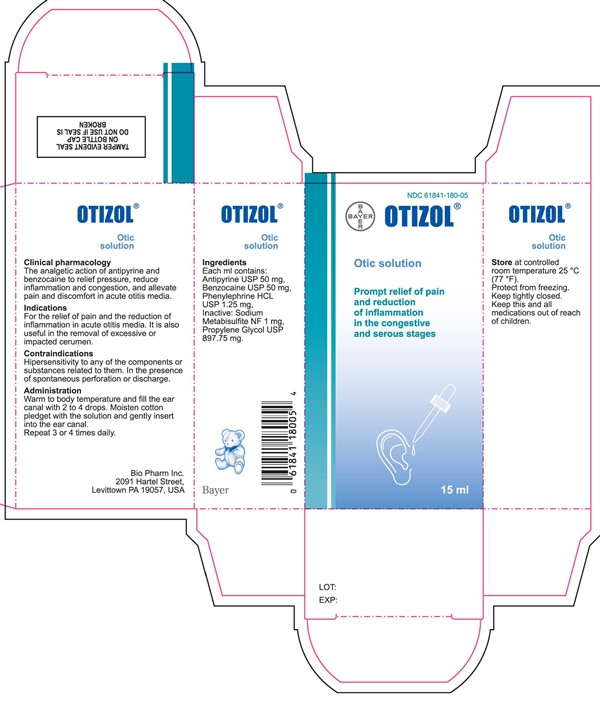 DRUG LABEL: Ortizol
NDC: 61841-180 | Form: LIQUID
Manufacturer: Bayer HealthCare LLC, Consumer Care
Category: otc | Type: HUMAN OTC DRUG LABEL
Date: 20150205

ACTIVE INGREDIENTS: ANTIPYRINE 50 mg/1 mL; BENZOCAINE 50 mg/1 mL; PHENYLEPHRINE HYDROCHLORIDE 1.25 mg/1 mL
INACTIVE INGREDIENTS: SODIUM METABISULFITE; PROPYLENE GLYCOL

Ortizol-Otic Solution

Each ml contains:

Antipyrine USP 50 mg

Benzocaine USP 50 mg

Phenylephrine HCL USP 1.25 mg

PURPOSE

The analgetic action of antipyrine and

benzocaine to relief pressure. reduce

inflammation and congestion. and allevate

pain and discomfort in acute otitis media.

INDICATIONS AND USAGE

For the relief of pain and the reduction of

inflammation in acute otitis media. It is also

useful in the removal of excessive or

impacted cerumen.

WARNINGS

Hipersensitivity to any of the components or

substances related to them. In the presence

of spontaneous perforation or discharge.

DOSAGE AND ADMINISTRATION

Warm to body temperature and fill the ear

canal with 2 to 4 drops. Moisten cotton

pledget with the solution and gently insert

into the ear canal.

Repeat 3 or 4 times daily.

OTHER SAFETY INFORMATION

Store at controlled

room temperature 25 °C

(77 ºF).

Protect from freezing.

Keep tightly closed.

Keep this and all

medications out of reach

of children.

INACTIVE INGREDIENT

Sodium

Metabisulfite NF 1 mg.

Propylene Glycol USP

897.75 mg.